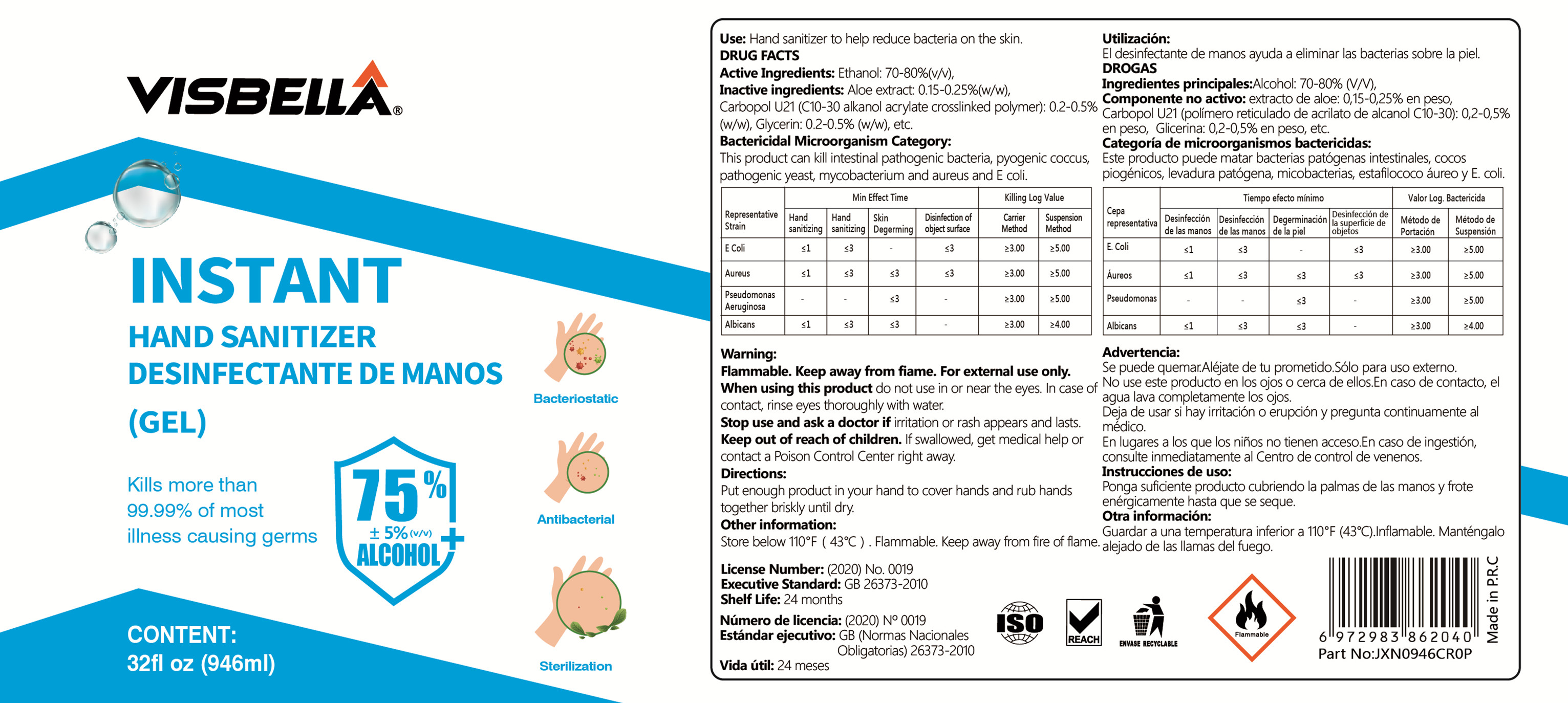 DRUG LABEL: Hand Sanitizer
NDC: 40760-015 | Form: GEL
Manufacturer: Huzhou Guoneng New Material Co., Ltd.
Category: otc | Type: HUMAN OTC DRUG LABEL
Date: 20200708

ACTIVE INGREDIENTS: ALCOHOL 709.5 mL/946 mL
INACTIVE INGREDIENTS: CARBOMER HOMOPOLYMER, UNSPECIFIED TYPE; WATER; ALOE; GLYCERIN; CHAMOMILE; TROLAMINE

DOSAGE AND ADMINISTRATION

Store below 110°F. Avoid direct sunlight,fluorescent lighting, heat, and moisture.

INACTIVE INGREDIENT

aloe extract

Carbomer U21 （C10-30 alkanol acrylate cross-linked polymer）

glycerin

Pure Water

Chamomile Scent

Triethanolamine

INDICATIONS AND USAGE

1.Adults and children over 2 years: Supervise children when they use this produc

2.For occasional andpersonal domestic use.

3.Rub thoroughly into hands for at least 30 seconds. Alow to dry.

ACTIVE INGREDIENT

Ethyl Alcohol

keep out of reach of children

PURPOSE

Disinfection
Sterilization

WARNINGS

1.For external use only
2.When using this product avoid contact with eyes. If contact occurs, rinse thoroughly with water.
3.Stop use and ask 1 consult a doctor 1 physician 1 health care practitioner I health care provider/ health care professional if iritation develops.
4..Keep out of reach of children.If swallowed, call a poison control cente or get medical help right away,